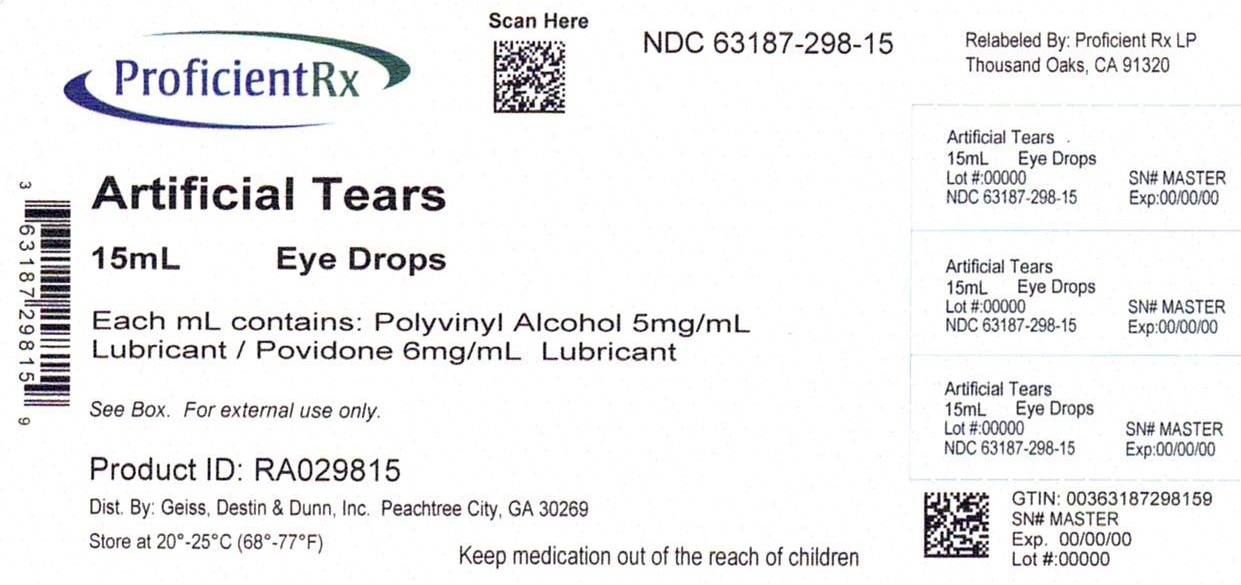 DRUG LABEL: GOODSENSE ARTIFICIAL TEARS
NDC: 63187-298 | Form: SOLUTION
Manufacturer: Proficient Rx LP
Category: otc | Type: HUMAN OTC DRUG LABEL
Date: 20240201

ACTIVE INGREDIENTS: POLYVINYL ALCOHOL, UNSPECIFIED 5 mg/1 mL; POVIDONE, UNSPECIFIED 6 mg/1 mL
INACTIVE INGREDIENTS: BENZALKONIUM CHLORIDE; DEXTROSE, UNSPECIFIED FORM; EDETATE DISODIUM; POTASSIUM CHLORIDE; WATER; SODIUM BICARBONATE; SODIUM CHLORIDE; SODIUM CITRATE, UNSPECIFIED FORM; SODIUM PHOSPHATE

Drug Facts

Uses

- temporary relieves burning and irritations due to dryness of the eye(s)
- protects against further irritation

Warnings

For external use only. Do not use if solution changes color or becomes cloudy or if you are sensitive to any ingredient in this product.

When using this product

- remove contact lenses before using
- do not touch tip of container to any surface to avoid contamination
- replace cap after each use

Stop use and ask a doctor if

- you feel eye pain
- changes in vision occur
- redness or irritation of the eye gets worse or lasts more than 72 hours

If pregnant or breast-feeding,

ask a health professional before use.

Keep out of the reach of children.

If swallowed, get medical help or contact a Poison Control Center right away.

Directions

- Instill 1 or 2 drops in the affected eye(s) as needed.
- Store at 15-25C (59-77F).
- Children under 6 years of age: Ask a doctor

Dosage and Administration

- Instill 1 or 2 drops in the affected eye(s) as needed.

Active Ingredient

Each mL contains: Polyvinyl Alcohol 5mg/ml and Povidone 6mg/ml - lubricant

INACTIVE INGREDIENT

Inactive Ingredients: Benzalkonium Chloride, Dextrose, Disodium Edetate, Potassium Chloride, Purified Water, Sodium Bicarbonate, Sodium Chloride, Sodium Citrate, Sodium Phosphate (Mono- and Dibasic)

PACKAGE LABEL

Relabeled By:

Proficient Rx LP

Thousand Oaks, CA 91320